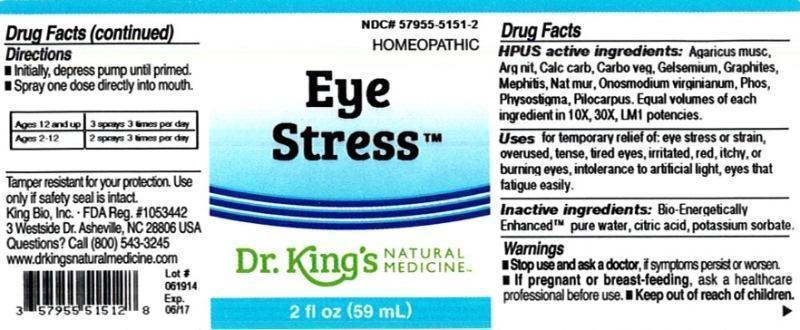 DRUG LABEL: Eye Stress
NDC: 57955-5151 | Form: LIQUID
Manufacturer: King Bio Inc.
Category: homeopathic | Type: HUMAN OTC DRUG LABEL
Date: 20140717

ACTIVE INGREDIENTS: AMANITA MUSCARIA FRUITING BODY 10 [hp_X]/59 mL; SILVER NITRATE 10 [hp_X]/59 mL; OYSTER SHELL CALCIUM CARBONATE, CRUDE 10 [hp_X]/59 mL; ACTIVATED CHARCOAL 10 [hp_X]/59 mL; GELSEMIUM SEMPERVIRENS ROOT 10 [hp_X]/59 mL; GRAPHITE 10 [hp_X]/59 mL; MEPHITIS MEPHITIS ANAL GLAND FLUID 10 [hp_X]/59 mL; SODIUM CHLORIDE 10 [hp_X]/59 mL; ONOSMODIUM VIRGINIANUM WHOLE 10 [hp_X]/59 mL; PHOSPHORUS 10 [hp_X]/59 mL; PHYSOSTIGMA VENENOSUM SEED 10 [hp_X]/59 mL; PILOCARPUS JABORANDI LEAF 10 [hp_X]/59 mL
INACTIVE INGREDIENTS: WATER; CITRIC ACID MONOHYDRATE; POTASSIUM SORBATE

Eye Stress™

ACTIVE INGREDIENT

Drug Facts__________________________________________________________________________________________________________

HPUS activeingredients: Agaricus muscarius, Argentum nitricum, Calcarea carbonica, Carbo vegetabilis, Gelsemium sempervirens, Graphites, Mephitis mephitica, Natrum muriaticum, Onosmodium virginianum, Phosphorus, Physostigma venenosum, Pilocarpus. Equal volumes of each ingredient in 10X, 30X, LM1 potencies.

INDICATIONS AND USAGE

Uses for temporary relief of: eye stress or strain, overused, tense, tired eyes, irritated, red, itchy, or burning eyes, intolerance to artificial light, eyes that fatigue easily.

Inactive Ingredients:

Bio-Energetically Enhanced™ pure water, citric acid and potassium sorbate.

Warnings

- Stop use and ask your doctor if symptoms persist or worsen.
- If pregnant or breast-feeding, ask a healthcare professional before use.

- Keep out of reach of children

Directions

- Initially, depress pump until primed.
- Spray one dose directly into mouth.
- Adults 12 and up: 3 sprays 3 times per day.
- Ages 2-12: 2 sprays 3 times per day.

OTHER SAFETY INFORMATION

Tamper resistant for your protection. Use only if safety seal is intact.

PURPOSE

Uses for temporary relief of:

- eye stress or strain
- overused, tense, tired eyes
- irritated, red, itchy, or burning eyes
- intolerance to artificial light
- eyes that fatigue easily